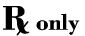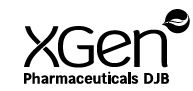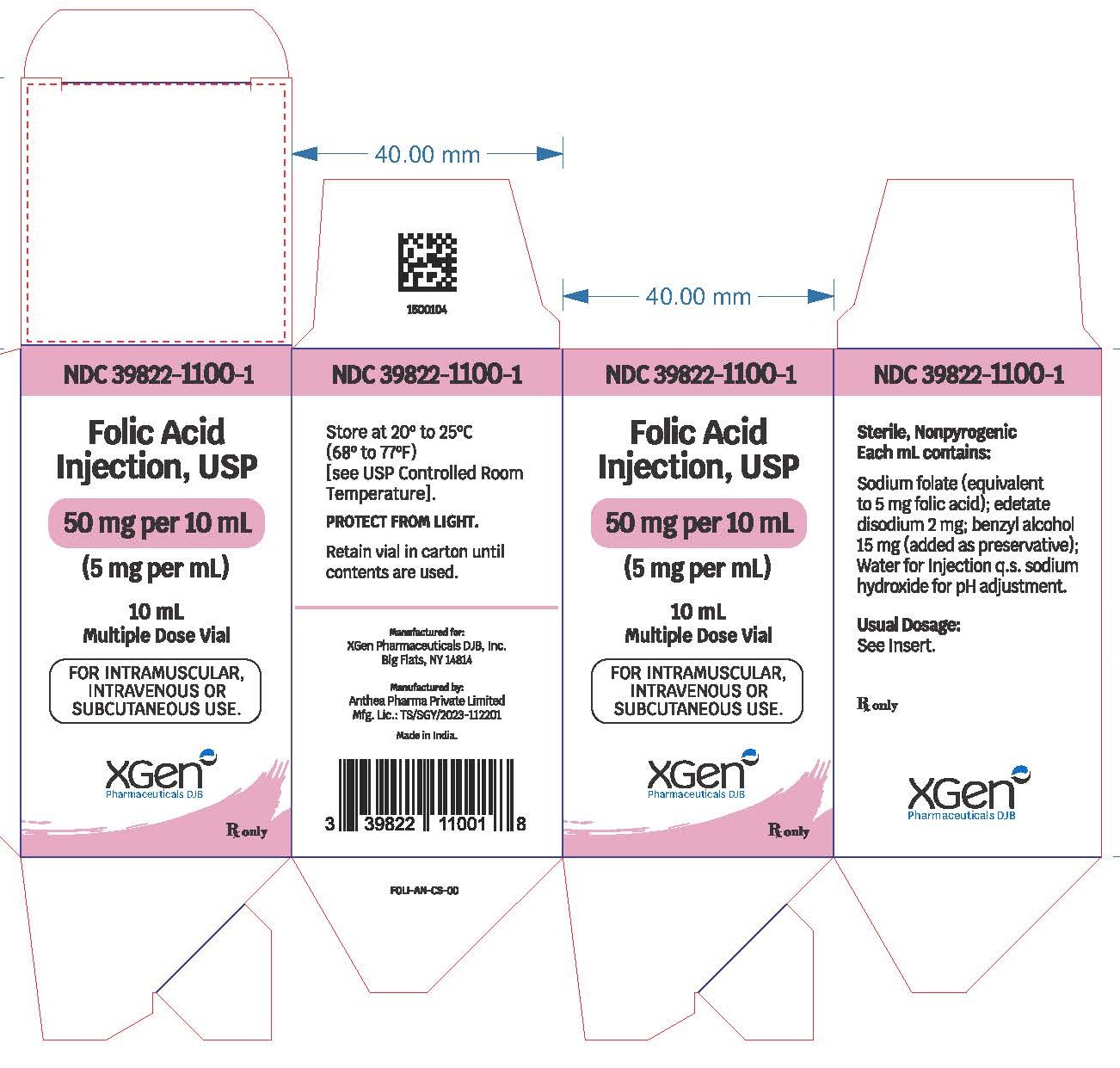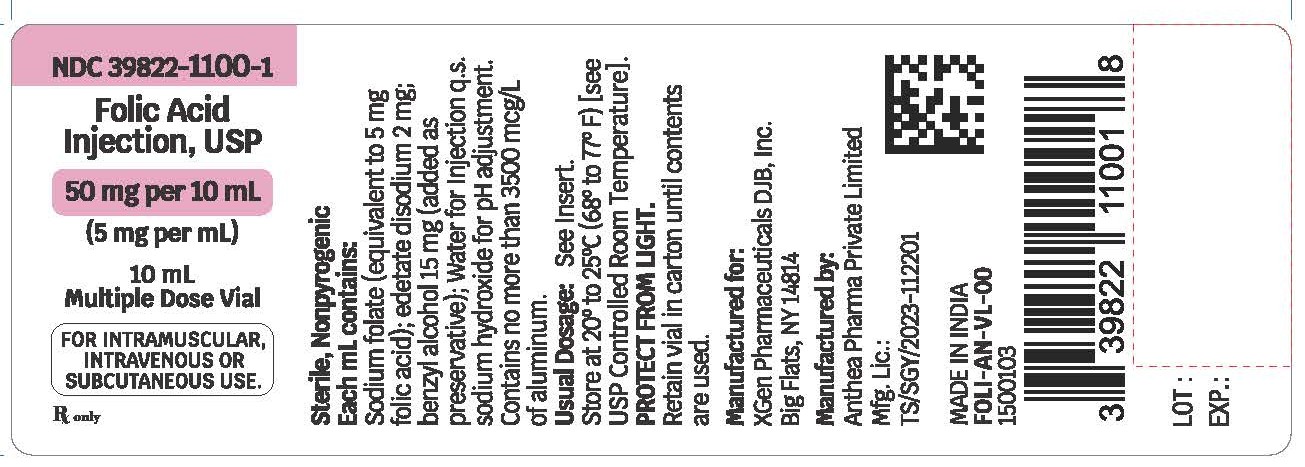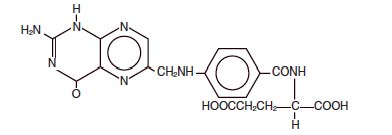 DRUG LABEL: Folic Acid
NDC: 39822-1100 | Form: INJECTION, SOLUTION
Manufacturer: XGen Pharmaceuticals DJB, Inc.
Category: prescription | Type: HUMAN PRESCRIPTION DRUG LABEL
Date: 20260121

ACTIVE INGREDIENTS: FOLIC ACID 5 mg/1 mL
INACTIVE INGREDIENTS: EDETATE SODIUM 2 mg/1 mL; BENZYL ALCOHOL 15 mg/1 mL; SODIUM HYDROXIDE

Folic Acid Injection, USP

DESCRIPTION

Folic Acid Injection, USP is a sterile, nonpyrogenic solution of sodium folate (prepared by the addition of sodium hydroxide to folic acid) in Water for Injection, USP intended for intramuscular (IM), intravenous (IV) or subcutaneous (SC) use.

Folic acid is a complex organic compound present in liver, yeast and other substances, which may be prepared synthetically. It is a yellow or yellowish orange, odorless crystalline powder. It is very slightly soluble in water, insoluble in alcohol, chloroform, ether; readily dissolves in dilute solutions of alkali hydroxides and carbonates. It is chemically designated as: L-Glutamic acid, N-[4-[[(2-amino-1-4-dihydro-4-oxo-6-pteridinyl) methyl] amino]benzoyl]-, and has the following structural formula.

C19H19N7O6 ; M.W. 441.40

Each mL contains: Sodium folate (equivalent to 5 mg folic acid); edetate disodium 2 mg; benzyl alcohol 15 mg (added as preservative); Water for Injection, USP q.s. Sodium hydroxide for pH adjustment (8.0 to 11.0).

CLINICAL PHARMACOLOGY

In man, an exogenous source of folate is required for nucleoprotein synthesis and maintenance of normal erythropoiesis. Folic acid, whether given by mouth or parenterally, stimulates specifically the production of red blood cells, white blood cells and platelets in persons suffering from certain megaloblastic anemias.

INDICATIONS AND USAGE

Folic Acid Injection, USP alone is effective in the treatment of megaloblastic anemias due to a deficiency of folic acid as may be seen in tropical or nontropical sprue, in anemias of nutritional origin, pregnancy, infancy or childhood.

WARNINGS

WARNING: This product contains aluminum that may be toxic. Aluminum may reach toxic levels with prolonged parenteral administration if kidney function is impaired. Premature neonates are particularly at risk because their kidneys are immature, and they require large amounts of calcium and phosphate solutions, which contain aluminum.

Research indicates that patients with impaired kidney function, including premature neonates, who receive parenteral levels of aluminum at greater than 4 to 5 mcg/kg/day accumulate aluminum at levels associated with central nervous system and bone toxicity. Tissue loading may occur at even lower rates of administration.

Folic acid alone is improper therapy in the treatment of pernicious anemia and other megaloblastic anemias where Vitamin B12 is deficient.

This product contains benzyl alcohol. Benzyl alcohol has been reported to be associated with a fatal “Gasping Syndrome” in premature infants.

PRECAUTIONS

Folic acid in doses above 0.1 mg daily may obscure pernicious anemia, in that hematologic remission can occur while neurological manifestations remain progressive.

ADVERSE REACTIONS

Allergic sensitization has been reported following both oral and parenteral administration of folic acid.

To report SUSPECTED ADVERSE REACTIONS, contact XGen Pharmaceuticals DJB, Inc. at 1-866- 390-4411 or FDA at 1-800-FDA-1088 or www.fda. gov/medwatch.

DOSAGE AND ADMINISTRATION

Parenteral Administration: Intramuscular (IM), intravenous (IV) and subcutaneous (SC) routes may be used if the disease is exceptionally severe or if gastrointestinal absorption may be, or is known to be, impaired.

Usual Therapeutic Dosage— In adults and children (regardless of age): up to 1 mg daily. Resistant cases may require larger doses.

Maintenance Level: When clinical symptoms have subsided and the blood picture has become normal, a maintenance level should be used, i.e., 0.1 mg for infants and up to 0.3 mg for children under four years of age, 0.4 mg for adults and children four or more years of age, and 0.8 mg for pregnant and lactating women, per day, but never less than 0.1 mg per day. Patient should be kept under close supervision and adjustment of the maintenance level made if relapse appears imminent.

In the presence of alcoholism, hemolytic anemia, anticonvulsant therapy or chronic infection, the maintenance level may need to be increased.

Parenteral drug products should be inspected visually for particulate matter and discoloration prior to administration, whenever solution and container permit.

HOW SUPPLIED

Folic Acid Injection, USP 50 mg per 10 mL (5 mg per mL) is available as:

Product NDC: 39822-1100-1
10 mL Multiple Dose, in a flip-top vial, packaged individually.

Store at 20° to 25°C (68° to 77°F) [see USP Controlled Room Temperature].

PROTECT FROM LIGHT.

Retain vial in carton until contents are used.

Manufactured in India.

Manufactured by:
Anthea Pharma Private Limited
Mfg. Lic: TS/SGY/2023-112201

Manufactured for:
XGen Pharmaceuticals DJB, Inc.
Big Flats, NY 14814

Revised: August 2025

FOLI-AN-PI-00

1500105

PACKAGE LABEL

PACKAGE LABEL - PRINCIPAL DISPLAY - Folic Acid 10 mL Vial Label

NDC 39822-1100-1

Folic Acid Injection, USP

50 mg per 10 mL (5 mg per mL)

For intramuscular, intravenous or subcutaneous use.

10 mL Multiple Dose Vial

Rx only

PACKAGE LABEL - PRINCIPAL DISPLAY - Folic Acid 10 mL Vial Carton

NDC 39822-1100-1

Folic Acid Injection, USP

50 mg per 10 mL (5 mg per mL)

For intramuscular, intravenous or subcutaneous use.

10 mL Multiple Dose Vial

Rx only